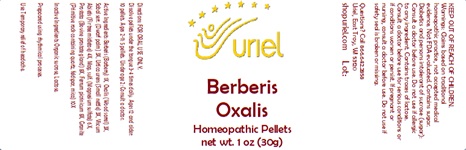 DRUG LABEL: Berberis Oxalis
NDC: 48951-2117 | Form: PELLET
Manufacturer: Uriel Pharmacy Inc.
Category: homeopathic | Type: HUMAN OTC DRUG LABEL
Date: 20241202

ACTIVE INGREDIENTS: FERROUS PICRATE 8 [hp_X]/1 1; BERBERIS VULGARIS ROOT BARK 1 [hp_X]/1 1; OXALIS STRICTA WHOLE 3 [hp_X]/1 1; SAW PALMETTO 3 [hp_X]/1 1; URTICA URENS 3 [hp_X]/1 1; VISCUM ALBUM FRUITING TOP 4 [hp_X]/1 1; MAGNESIUM SULFATE, UNSPECIFIED 6 [hp_X]/1 1; BOS TAURUS PROSTATE GLAND 8 [hp_X]/1 1; PENOXSULAM 10 [hp_X]/1 1
INACTIVE INGREDIENTS: LACTOSE; SUCROSE

Berberis Oxalis

INDICATIONS AND USAGE

Directions: FOR ORAL USE ONLY.

DOSAGE AND ADMINISTRATION

Dissolve pellets under the tongue 3-4
times daily. Ages 12 and older: 10 pellets.
Ages 2-11: 5 pellets. Under age 2: Consult
a doctor.

ACTIVE INGREDIENT

Active Ingredients: Berberis (Barberry) 1X,Oxalis (Wood sorrel) 3X, Sabal serr. (Dwarf palm) 3X, Urtica urens (Small nettle) 3X, Viscum Abietis (Fir tree mistletoe) 4X, Mag. sulf. (Magnesium sulfate) 6X, Prostata (Bovine prostate gland) 8X,Ferrum picrinicum 8X,Granite (Primitive rock containing quartz, feldspar, mica) 10X

Inactive Ingredients: Organic sucrose, Lactose.

Prepared using rhythmical processes.

PURPOSE

Use: Temporary relief of headache.

KEEP OUT OF REACH OF CHILDREN.

WARNINGS

Warnings: Claims based on traditional homeopathic practice, not accepted medical evidence. Not FDA evaluated. Contains sugar. Diabetics and persons intolerant of sucrose (sugar): Consult a doctor before use. Do not use if allergic to any ingredient. Contains traces of lactose. Consult a doctor before use for serious conditions or if conditions worsen or persist. If pregnant or nursing, consult a doctor before use. Do not use if safety seal is broken or missing.

Questions? Call 866.642.2858
Uriel, East Troy, WI 53120
shopuriel.com